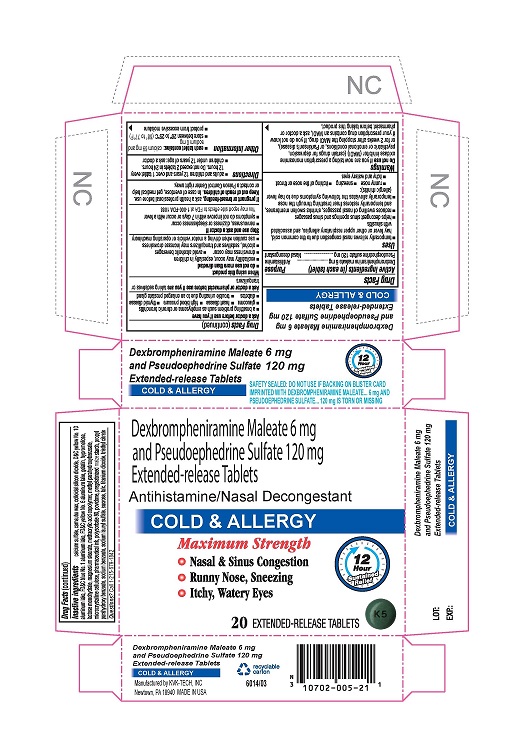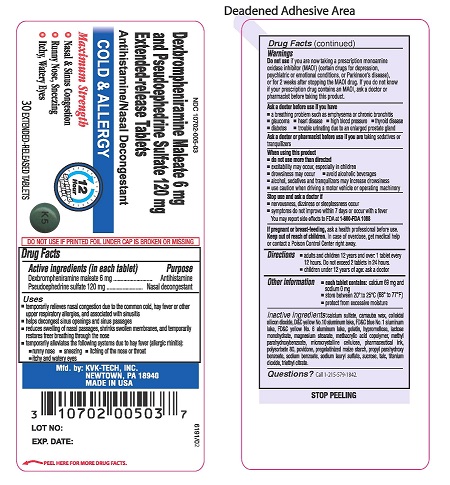 DRUG LABEL: Dexbrompherniramine Maleate and Pseudoephedrine Sulfate
NDC: 10702-005 | Form: TABLET, EXTENDED RELEASE
Manufacturer: KVK-TECH, INC.
Category: otc | Type: HUMAN OTC DRUG LABEL
Date: 20171204

ACTIVE INGREDIENTS: DEXBROMPHENIRAMINE MALEATE 6 mg/1 1; PSEUDOEPHEDRINE SULFATE 120 mg/1 1
INACTIVE INGREDIENTS: CALCIUM SULFATE; CARNAUBA WAX; SILICON DIOXIDE; D&C YELLOW NO. 10; FD&C BLUE NO. 1; FD&C YELLOW NO. 6; GELATIN; HYPROMELLOSES; LACTOSE MONOHYDRATE; MAGNESIUM STEARATE; METHACRYLIC ACID - METHYL METHACRYLATE COPOLYMER (1:1); METHYLPARABEN; CELLULOSE, MICROCRYSTALLINE; POLYSORBATE 80; POVIDONE; STARCH, CORN; PROPYLPARABEN; SODIUM BENZOATE; SODIUM LAURYL SULFATE; SUCROSE; TALC; TITANIUM DIOXIDE; TRIETHYL CITRATE

Dexbrompheniramine maleate 6 mg
Pseudoephedrine Sulfate 120 mg

DRUG FACTS

ACTIVE INGREDIENT (IN EACH TABLET)

Dexbrompheniramine maleate 6 mg

Pseudoephedrine Sulfate 120 mg

PURPOSE

Antihistamine

Nasal decongestant

USES

- temporarily relieves nasal congestion due to the common cold, hay fever or other upper respiratory allergies, and associated with sinusitis
- helps decongest sinus openings and sinus passages
- reduces swelling of nasal passages, shrinks swollen membranes, and temporarily restores freer breathing through the nose
- temporarily alleviates the following symptoms due to hay fever (allergic rhinitis):
  - runny nose
  - sneezing
  - itching of the nose or throat
  - itchy and watery eyes

WARNINGS

Do not use If you are now taking a prescription monoamineoxidase inhibitor (MAOI) (certain drugs for depression, psychiatric or emotional conditions, or Parkinson’s disease), or for 2 weeks after stopping the MAOI drug. If you do not know if your prescription drug contains an MAOI, ask a doctor or pharmacist before taking this product.

ASK A DOCTOR BEFORE USE IF YOU HAVE

- a breathing problem such as emphysema or chronic bronchitis
- glaucoma
- heart disease
- high blood pressure
- thyroid disease
- diabetes
- trouble urinating due to an enlarged prostate gland

ASK DOCTOR/PHARMACIST BEFORE USE IF YOU ARE

- taking sedative or tranquilizers

WHEN USING THIS PRODUCT

- do not use more than directed
- excitability may occur, especially in children
- drowsiness may occur
- avoid alcoholic beverages
- alcohol, sedatives, and tranquilizers may increase drowsiness
- use caution when driving a motor vehicle or operating machinery

STOP USE AND ASK A DOCTOR IF

- nervousness, dizziness or sleeplessness occur
- symptoms do not improve within 7 days or occur with a fever

You may report side effects to FDA at 1-800-FDA 1088

IF PREGNANT OR BREAST-FEEDING

ask a health professional before use.

KEEP OUT OF REACH OF CHILDREN

In case of overdose, get medical help or contact a Poison Control Center right away.

DIRECTIONS

- adults and children 12 years and over: 1 tablet every 12 hours. Do not exceed 2 tablets in 24 hours.
- children under 12 years of age: ask a doctor

OTHER INFORMATION

- each tablet contains: calcium 69 mg and sodium 0 mg
- store between 20° to 25°C (68° to 77°F)
- protect from excessive moisture

INACTIVE INGREDIENTS

calcium sulfate, carnauba wax, colloidal silicon dioxide, D&C yellow No. 10 aluminum lake, FD&C blue No. 1 aluminum lake, FD&C yellow No. 6 aluminum lake, gelatin, hypromellose, lactose monohydrate, magnesium stearate, methacrylic acid copolymer, methyl parahydroxybenzoate, microcrystalline cellulose, pharmaceutical ink, polysorbate 80, povidone, pregelatinized maize starch, propyl parahydroxy benzoate, sodium benzoate, sodium lauryl sulfate, sucrose, talc, titanium dioxide, triethyl citrate

QUESTIONS

call 1-215-579-1842

PRODUCT PACKAGING

The product packaging shown below represents a sample of that currently in use. Additional packaging may also be available.

Dexbrompheniramine Maleate 6 mg

and Pseudoephedrine Sulfate 120 mg

Extended-release Tablets

Antihistamine/Nasal Decongestant

COLD & ALLERGY

Maximum Strength

- Nasal & Sinus Congestion
- Runny Nose, Sneezing
- Itchy, Watery Eyes
  12 Hour Sustained Relief
  20 EXTENDED-RELEASE TABLETS
  SAFETY SEALED: DO NOT USE IF BACKING ON BLISTER CARD IMPRINTED WITH DEXBROMPHENIRAMINE MALEATE 6 mg AND PSEUDOEPHEDRINE SULFATE 120 mg IS TORN OR MISSING.
  Manufactured by KVK-TECH, INC.
  Newtown, PA18940 MADE IN USA

Principal Display Panel

Carton Label

Dexbrompheniramine Maleate 6 mg
and Pseudoephedrine Sulfate 120 mg
Extended-release Tablets

Antihistamine/Nasal Decongestant

COLD & ALLERGY

Maximum Strength

- Nasal & Sinus Congestion
- Runny Nose, Sneezing
- Itchy, Watery Eyes12 Hour Sustained Relief

20 EXTENDED-RELEASE TABLETS

Container Label

NDC 10702-005-03

Dexbrompheniramine Maleate 6 mg
and Pseudoephedrine Sulfate 120 mg
Extended-release Tablets

Antihistamine/Nasal Decongestant

COLD & ALLERGY

Maximum Strength

- Nasal & Sinus Congestionunny Nose, Sneezing
- Itchy, Watery Eyes12 Hour Sustained Relief

30 EXTENDED-RELEASE TABLETS

DO NOT USE IF PRINTED FOIL UNDER CAP IS BROKEN OR MISSING.